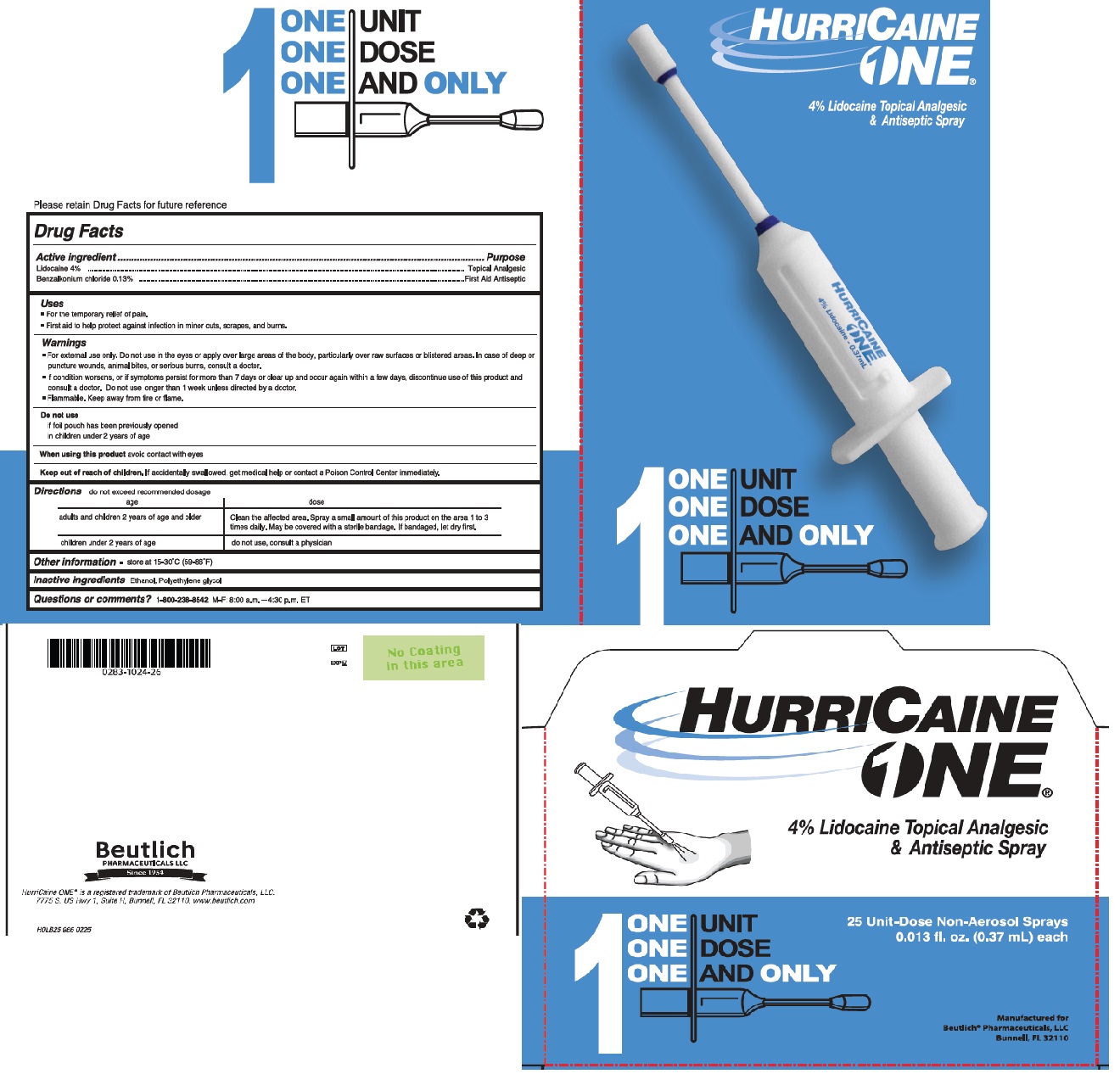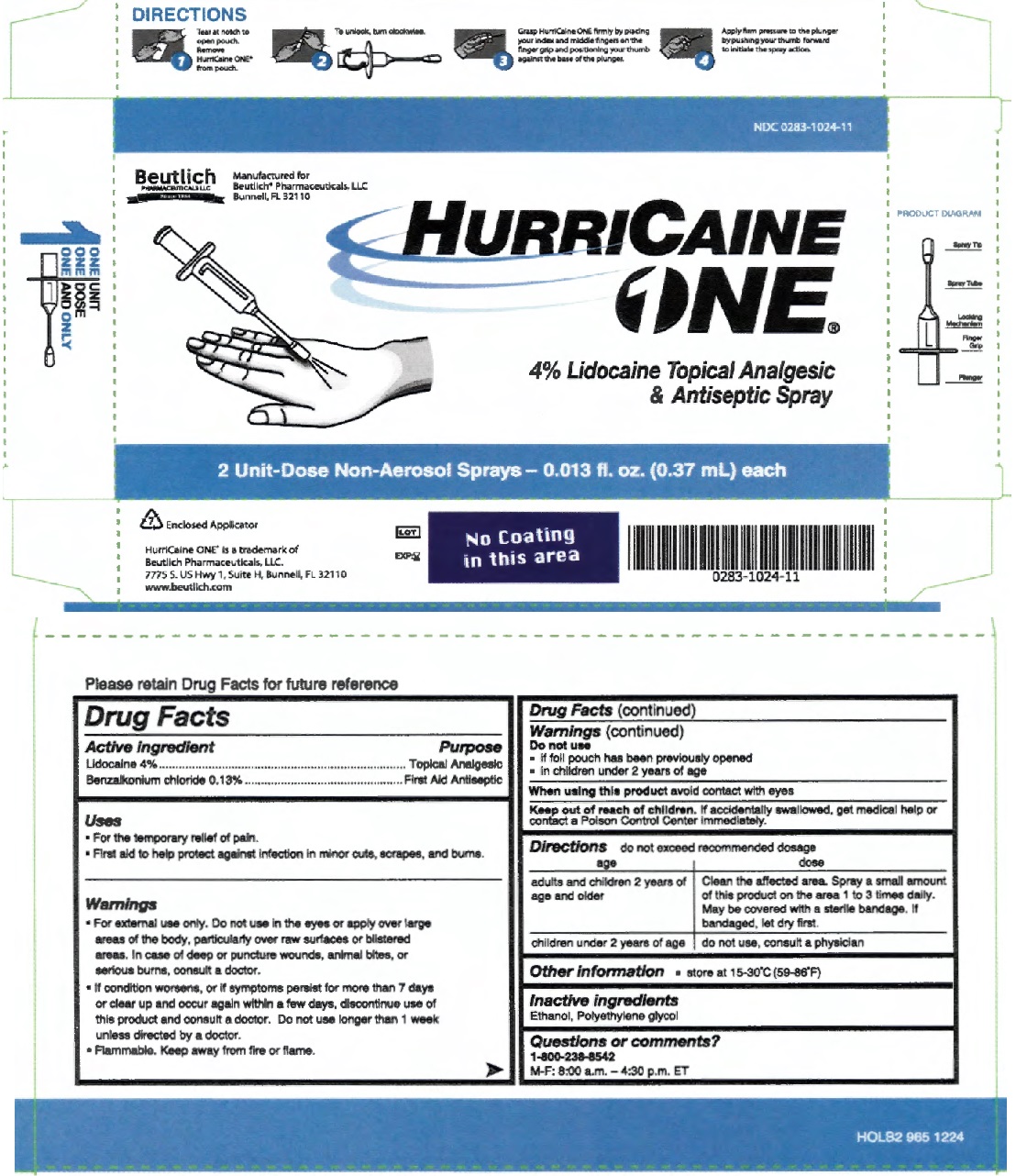 DRUG LABEL: HurriCaine One
NDC: 0283-1024 | Form: SPRAY
Manufacturer: Beutlich Pharmaceuticals LLC
Category: otc | Type: HUMAN OTC DRUG LABEL
Date: 20251210

ACTIVE INGREDIENTS: LIDOCAINE HYDROCHLORIDE 40 mg/1 g; BENZALKONIUM CHLORIDE 1.3 mg/1 g
INACTIVE INGREDIENTS: POLYETHYLENE GLYCOL 400 200 mg/1 g; ALCOHOL 758.7 mg/1 g

HC1 - Lidocaine
Drug Facts

Active Ingredients

Lidocaine 4%

Benzalkonium Chloride 0.13%

Purpose

Topical Anesthetic/Analgesic

Topical First-Aid Antiseptic

Uses

- For the temporary relief of pain
- First aid to help protect against infection in minor cuts, scrapes, and burns

Warnings

- For external use only. Do not use In the eyes or apply over large areas of the body, particularly over raw sur1aces or blistered areas. In case of deep or puncture wounds, animal bites, or serious burns, consult a doctor.
- If condition worsens, or If symptoms persist for more than 7 days or clear up and occur again within a few days, discontinue use of this product and consult a doctor. Do not use longer than 1 week unless directed by a doctor.
- Flammable. Keep away from fire or flame.

Do not use

- if foil pouch has been previously opened
- in children under 2 years of age

When using this product

- avoid contact with eyes

Keep out of reach of children.

If more than used for pain is accidently swallowed, get medical help or contact a Poison Control Center Immediately

Directions

- do not exceed recommended dosage

adults and children 2 years of age and older: Clean the affected area. Spray a small amount of this product on the area 1 to 3 times dally. May be covered wtth a sterile bandage. If bandaged, let dry first.

children under 2 years of age: do not use, consult a physician

Other information

- store at 15-30 °C (59-86 °F)

Inactive ingredients

Polyethylene glycol, Ethanol

Questions or comments?

1-800-238-4582

M-F: 8:00 a.m. - 4:30 p.m. ET